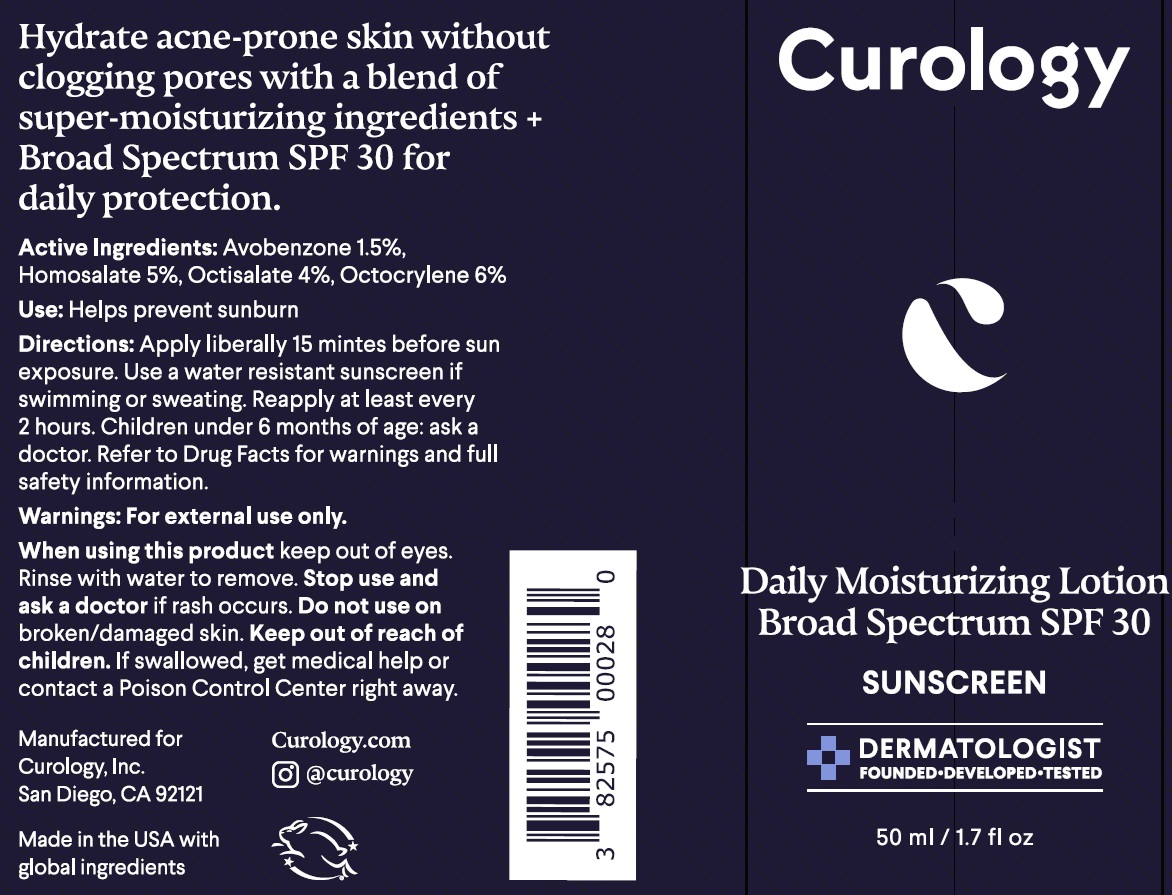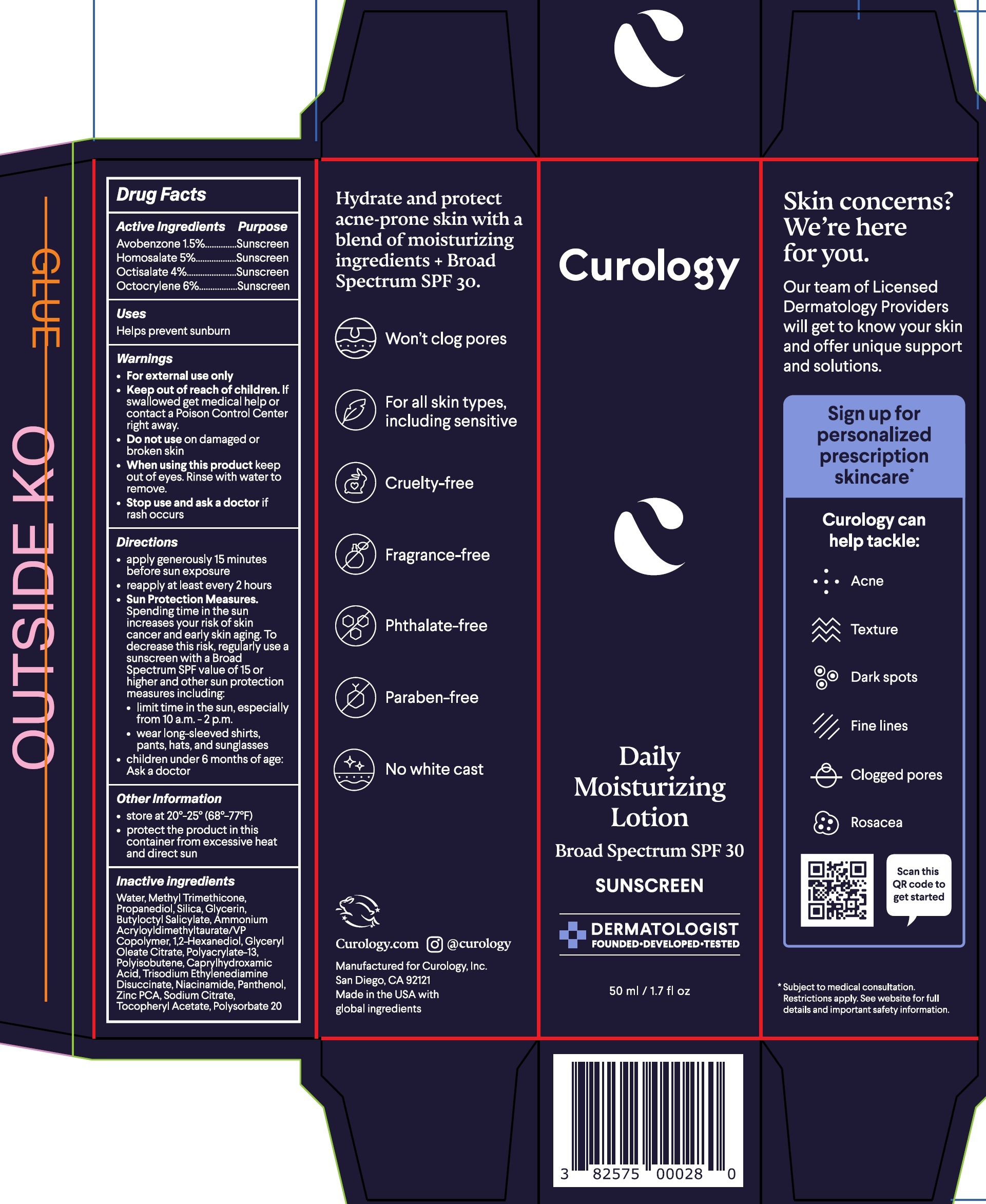 DRUG LABEL: Curology Daily Moisturizing Sunscreen SPF 30
NDC: 82575-036 | Form: CREAM
Manufacturer: Curology
Category: otc | Type: HUMAN OTC DRUG LABEL
Date: 20251015

ACTIVE INGREDIENTS: AVOBENZONE 15 mg/1 mL; HOMOSALATE 50 mg/1 mL; OCTISALATE 40 mg/1 mL; OCTOCRYLENE 60 mg/1 mL
INACTIVE INGREDIENTS: WATER; METHYL TRIMETHICONE; PROPANEDIOL; SILICON DIOXIDE; GLYCERIN; BUTYLOCTYL SALICYLATE; AMMONIUM ACRYLOYLDIMETHYLTAURATE/VP COPOLYMER; 1,2-HEXANEDIOL; GLYCERYL MONOOLEATE CITRATE; POLYACRYLATE-13; CAPRYLHYDROXAMIC ACID; TRISODIUM ETHYLENEDIAMINE DISUCCINATE; NIACINAMIDE; PANTHENOL; ZINC PIDOLATE; SODIUM CITRATE, UNSPECIFIED FORM; .ALPHA.-TOCOPHEROL ACETATE; POLYSORBATE 20

Curology Daily Moisturizing Lotion Sunscreen SPF 30 (82575-036-00)

Active ingredients

Avobenzone 1.5%
Homosalate 5%
Octisalate 4%
Octocrylene 6%

Purpose

Sunscreen

Uses

Helps prevent sunburn

Warnings

For external use only.

Keep out of reach of children.

If swallowed, get medical help or contact a Poison Control Center right away.

Do not use

on damaged or broken skin.

When using this product

keep out of eyes. Rinse with water to remove.

Stop use and ask a doctor

if rash occurs.

Directions

- apply generously 15 minutes before sun exposure
- reapply at least every 2 hours
- Sun Protection Measures.Spending time in the sun increases your risk of skin cancer and early skin aging. To decrease this risk, regularly use a sunscreen with a Broad Spectrum SPF value of 15 or higher and other sun protection measures including:
- limit time in the sun, especially from 10 a.m.–2 p.m.
- wear long-sleeved shirts, pants, hats, and sunglasses
- children under 6 months of of age: Ask a doctor

Other information

- store at 20°-25° (68°-77°F)
- protect the product in this container from excessive heat and direct sun

Inactive ingredients

Water, Methyl Trimethicone, Propanediol, Silica, Glycerin, Butyloctyl Salicylate, Ammonium Acryloyldimethyltaurate/VP Copolymer, 1,2-Hexanediol, Glyceryl Oleate Citrate, Polyacrylate-13, Polyisobutene, Caprylhydroxamic Acid, Trisodium Ethylenediamine Disuccinate, Niacinamide, Panthenol, Zinc PCA, Sodium Citrate, Tocopheryl Acetate, Polysorbate 20